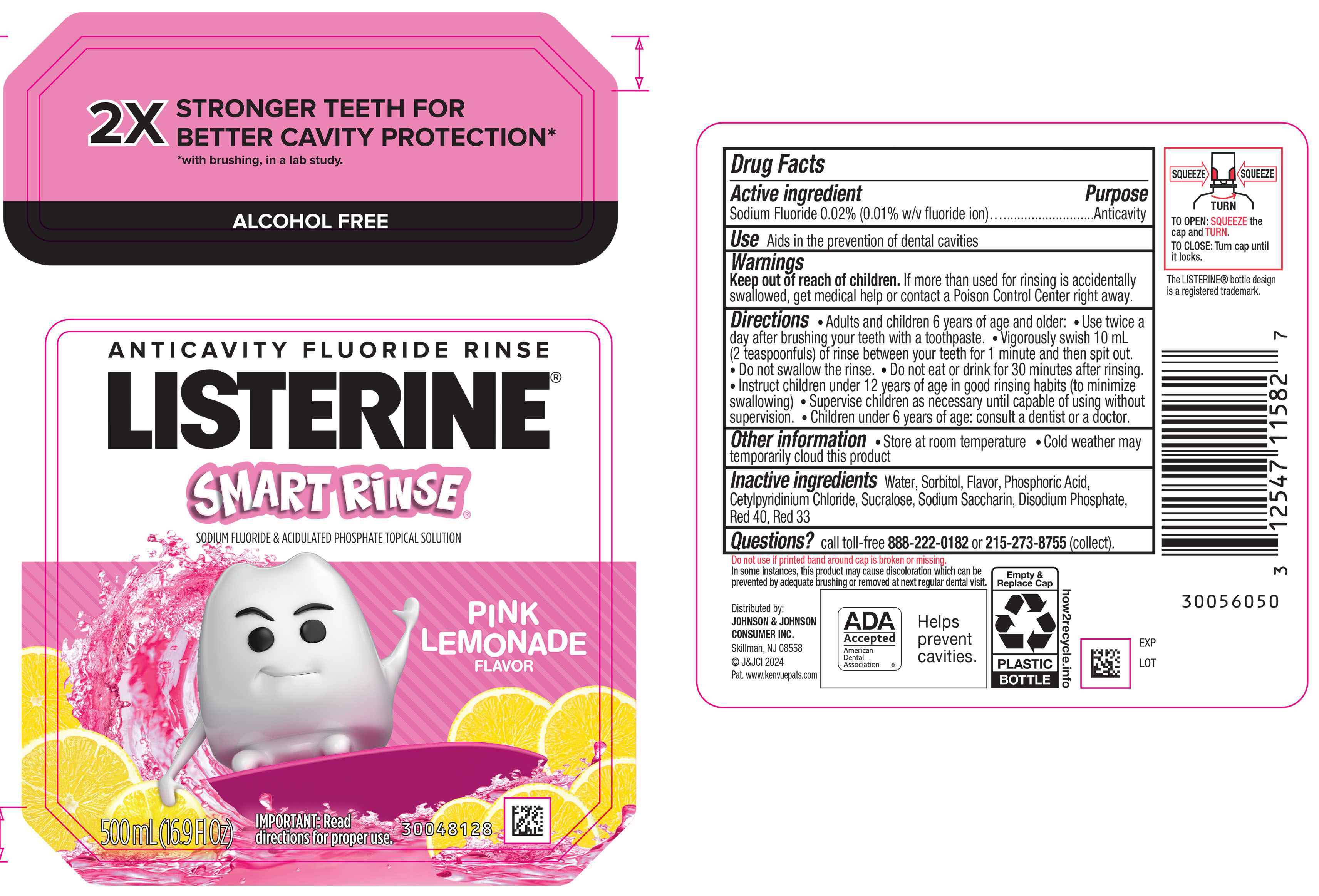 DRUG LABEL: Listerine Smart Rinse Anticavity Fluoride Rinse - Pink Lemonade Flavor
NDC: 69968-0691 | Form: MOUTHWASH
Manufacturer: Kenvue Brands LLC
Category: otc | Type: HUMAN OTC DRUG LABEL
Date: 20250723

ACTIVE INGREDIENTS: SODIUM FLUORIDE 0.1 mg/1 mL
INACTIVE INGREDIENTS: WATER; SORBITOL; PHOSPHORIC ACID; CETYLPYRIDINIUM CHLORIDE; SUCRALOSE; SACCHARIN SODIUM; SODIUM PHOSPHATE, DIBASIC, ANHYDROUS; FD&C RED NO. 40; D&C RED NO. 33

LISTERINE® SMART RINSE® ANTICAVITY FLUORIDE RINSE PINK LEMONADE FLAVOR

Drug Facts

Active ingredient

Sodium fluoride 0.02% (0.01% w/v fluoride ion)

Purpose

Anticavity

Use

Aids in the prevention of dental cavities

Warnings

Keep out of reach of children. If more than used for rinsing is accidentally swallowed, get medical help or contact a Poison Control Center right away.

Directions

- Adults and children 6 years of age and older:
  - Use twice a day after brushing your teeth with a toothpaste
  - Vigorously swish 10 mL (2 teaspoonfuls) of rinse between your teeth for 1 minute and then spit out
  - Do not swallow the rinse
  - Do not eat or drink for 30 minutes after rinsing
  - Instruct children under 12 years of age in good rinsing habits (to minimize swallowing)
  - Supervise children as necessary until capable of using without supervision
- Children under 6 years of age: consult a dentist or doctor

Other information

- Store at room temperature
- Cold weather may temporarily cloud this product

Inactive ingredients

Water, Sorbitol, Flavor, Phosphoric Acid, Cetylpyridinium Chloride, Sucralose, Sodium Saccharin, Disodium Phosphate, Red 40, Red 33

Questions?

call toll-free 888-222-0182 or 215-273-8755 (collect).

Distributed by:
JOHNSON & JOHNSON
CONSUMER INC.
Skillman, NJ 08558

PRINCIPAL DISPLAY PANEL - 500 mL Bottle Label

2X STRONGER TEETH FOR
BETTER CAVITY PROTECTION*
*with a brushing, in a lab study
ALCOHOL FREE

ANTICAVITY FLUORIDE RINSE
LISTERINE®

SMART RiNSE ®
SODIUM FLUORIDE & ACIDULATED PHOSPAHTE TOPICAL SOLUTION

PINK
LEMONADE
FLAVOR

500 mL (16.9Fl Oz)

IMPORTANT: Read
directions for proper use.